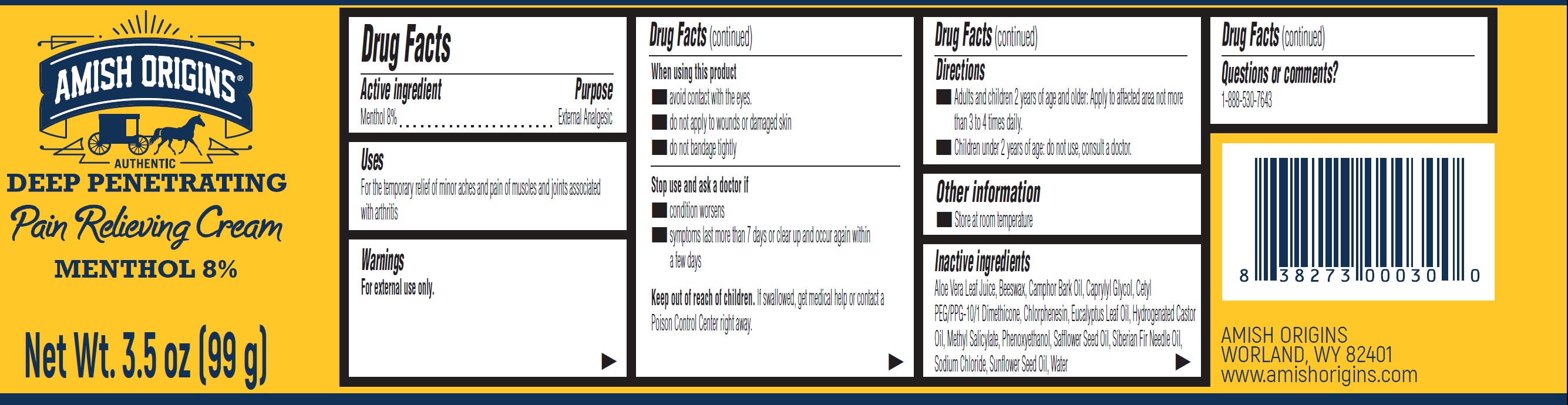 DRUG LABEL: Amish Origins Pain Relieving Menthol 8%
NDC: 62212-000 | Form: CREAM
Manufacturer: Amish Origins Management, LLC
Category: otc | Type: HUMAN OTC DRUG LABEL
Date: 20240229

ACTIVE INGREDIENTS: MENTHOL 80 mg/1 g
INACTIVE INGREDIENTS: ALOE VERA LEAF; YELLOW WAX; CAMPHOR OIL; CAPRYLYL GLYCOL; CHLORPHENESIN; EUCALYPTUS OIL; HYDROGENATED CASTOR OIL; METHYL SALICYLATE; PHENOXYETHANOL; SODIUM CHLORIDE; SUNFLOWER OIL; WATER

Amish Origins Pain Relieving Cream Menthol 8%

Active ingredient

Menthol 8%

Purpose

External Analgesic

Uses

For the temporary relief of minor aches and pain of muscles and joints associated with arthritis

Warnings

For external use only.

When using this product

- avoid contact with the eyes.
- do not apply to wounds or damaged skin
- do not bandage tightly

Stop use and ask a doctor if

- condition worsens
- symptoms last more than 7 days or clear up and occur again within a few days

Keep out of reach of children.

If swallowed, get medical help or contact a Poison Control Center right away.

Directions

- Adults and children 2 years of age and older: Apply to affected area not more than 3 to 4 times daily.

- Children under 2 years of age: do not use, consult a doctor.

Other information

- Store at room temperature

Inactive ingredients

Aloe Vera Leaf Juice, Beeswax, Camphor Bark Oil, Caprylyl Glycol, Cetyl PEG/PPG-10/1 Dimethicone, Chlorphenesin, Eucalyptus Leaf Oil, Hydrogenated Castor Oil, Methyl Salicylate, Phenoxyethanol, Safflower Seed Oil, Siberian Fir Needle Oil, Sodium Chloride, Sunflower Seed Oil, Water

Questions or comments?

1-888-530-7643